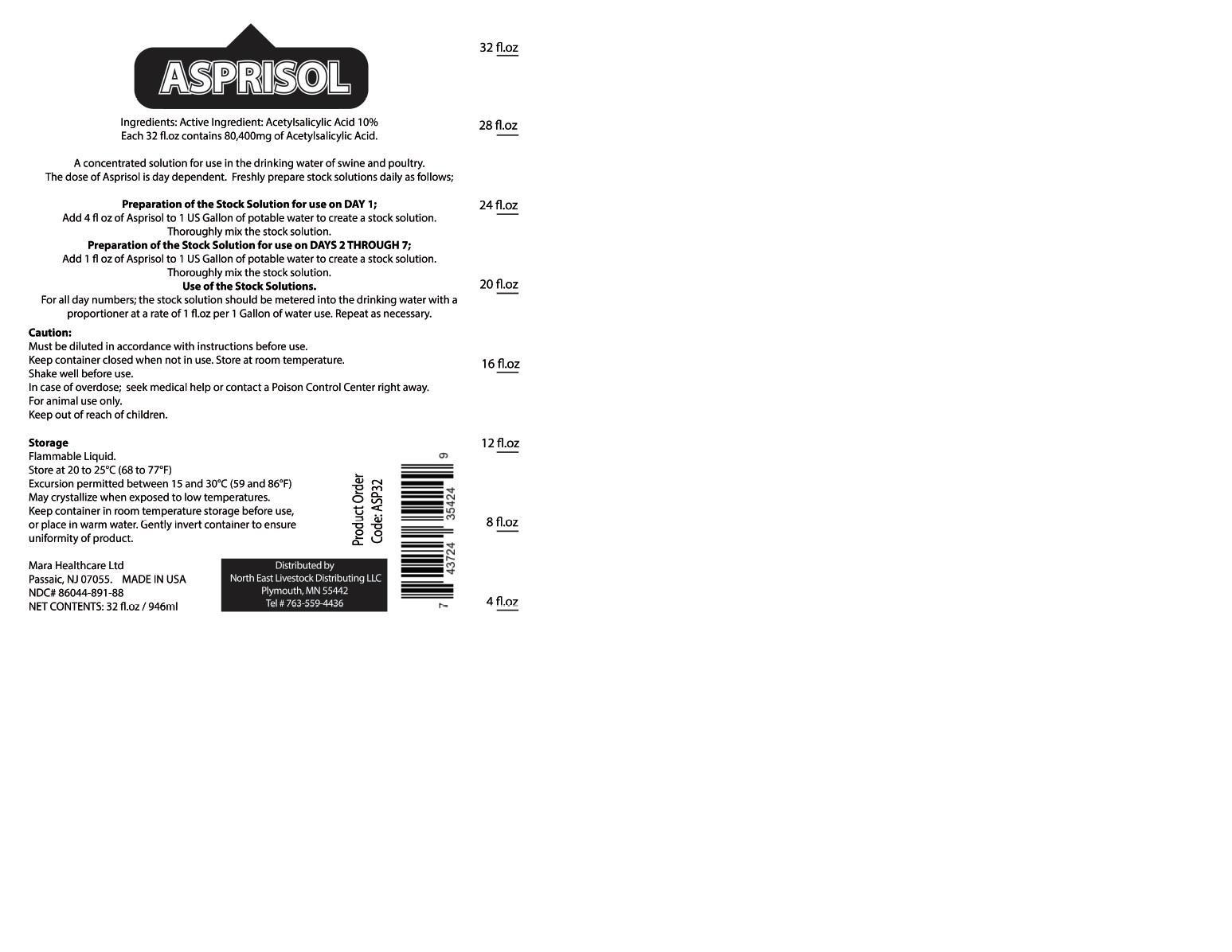 DRUG LABEL: ASPRISOL
NDC: 86044-891 | Form: LIQUID
Manufacturer: Mara Healthcare Ltd
Category: animal | Type: OTC ANIMAL DRUG LABEL
Date: 20150429

ACTIVE INGREDIENTS: ASPIRIN 85 mg/1 mL
INACTIVE INGREDIENTS: FD&C BLUE NO. 1; ALCOHOL; APPLE

ASPRISOL

PRECAUTIONS SECTION

Must be diluted in accordance with instructions before use.
Keep container closed when not in use. Store at room temperature.
Shake well before use. In case of overdose, get medical help or contact a Poison Control Center right away.
For animal use only.

PACKAGE LABEL.PRINCIPAL DISPLAY PANEL

Mara asprisol.jpg

DOSAGE & ADMINISTRATION SECTION

A concentrated solution for use in the drinking water of swine and poultry.
The dose of Asprisol is day dependent. Freshly prepare stock solutions daily as follows;
Preparation of the Stock Solution for use on DAY 1;
Add 4 fl oz of Asprisol to 1 US Gallon of potable water to create a stock solution. Thoroughly mix the stock solution.
Preparation of the Stock Solution for use on DAYS 2 THROUGH 7;
Add 1 fl oz of Asprisol to 1 US Gallon of potable water to create a stock solution. Thoroughly mix the stock solution.
Use of the Stock Solutions.
For all day numbers; the stock solution should be metered into the drinking water with a proportioner at a rate of 1 floz per 1 Gallon of water use.
Repeat as necessary.

OTC - KEEP OUT OF REACH OF CHILDREN

Keep out of reach of children.

OTC - ACTIVE INGREDIENT SECTION

Acetylsalicylic Acid

INACTIVE INGREDIENT SECTION

Ethanol

4-Methyl-2-pentanone

Hydroxymethane

2-Propanol

Color

Flavor

STORAGE AND HANDLING SECTION

Flammable Liquid.
Store at 20 to 25°C (68 to 77°F)
Excursion permitted between 15 and 30°C (59 and 86°F)
May crystallize when exposed to low temperatures. Keep container in room temperature storage before use, or place in warm water. Gently invert container to ensure uniformity of product.